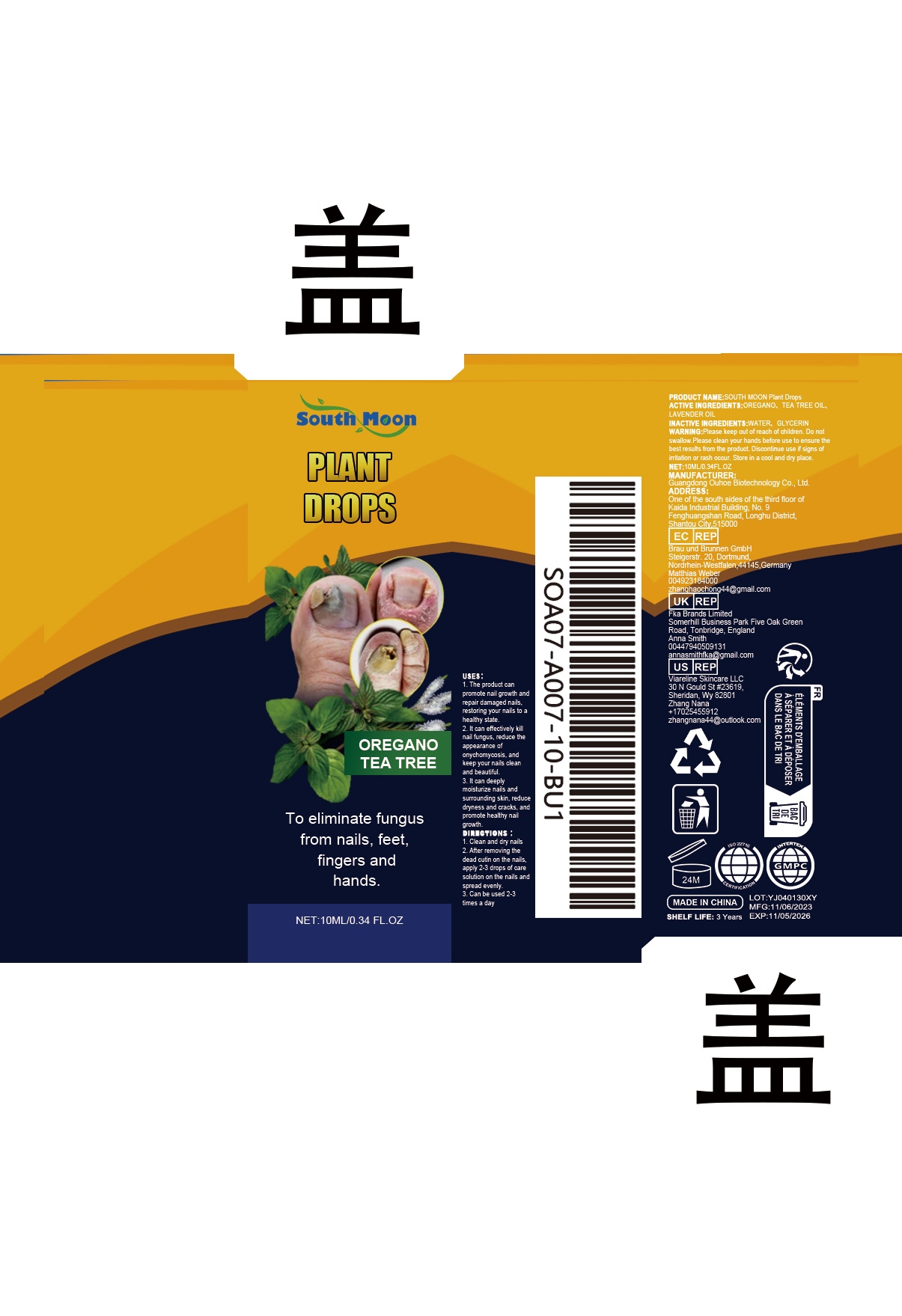 DRUG LABEL: SOUTH MOON Plant Drops
NDC: 84744-002 | Form: LIQUID
Manufacturer: Guangdong Ouhoe Biotechnology Co., Ltd.
Category: otc | Type: HUMAN OTC DRUG LABEL
Date: 20241105

ACTIVE INGREDIENTS: LAVENDER OIL 1 mg/10 mg; TEA TREE OIL 1 mg/10 mg; OREGANO 2 mg/10 mg
INACTIVE INGREDIENTS: WATER 4 mg/10 mg; GLYCERIN 2 mg/10 mg

Active Ingredient(s)

OREGANO、TEA TREE OIL、LAVENDER OIL

Purpose

1. The product can promote nail growth and repair damaged nails, restoring your nails to a healthy state.
2. It can effectively kill nail fungus, reduce the appearance of onychomycosis, and keep your nails clean and beautiful.
3. It can deeply moisturize nails and surrounding skin, reduce dryness and cracks, and promote healthy nail growth.

Use

1. Clean and dry nails
2. After removing the dead cutin on the nails, apply 2-3 drops of care solution on the nails and spread evenly.
3. Can be used 2-3 times a day

Warning

Please keep out of reach of children.Do not swallow.Please clean your hands before use to ensure the best results from the product.Discontinue use if signs of irritation or rash occur.Store in a cool and dry place.

Do not use

Discontinue use if signs of irritation or rash occur.

Stop use

Discontinue use if signs of irritation or rash occur.

KEEP OUT OF REACH OF CHILDREN

Please keep out of reach of children. Do not swallow.

STORAGE AND HANDLING

Store in a cool and dry place.

INACTIVE INGREDIENT

WATER、GLYCERIN